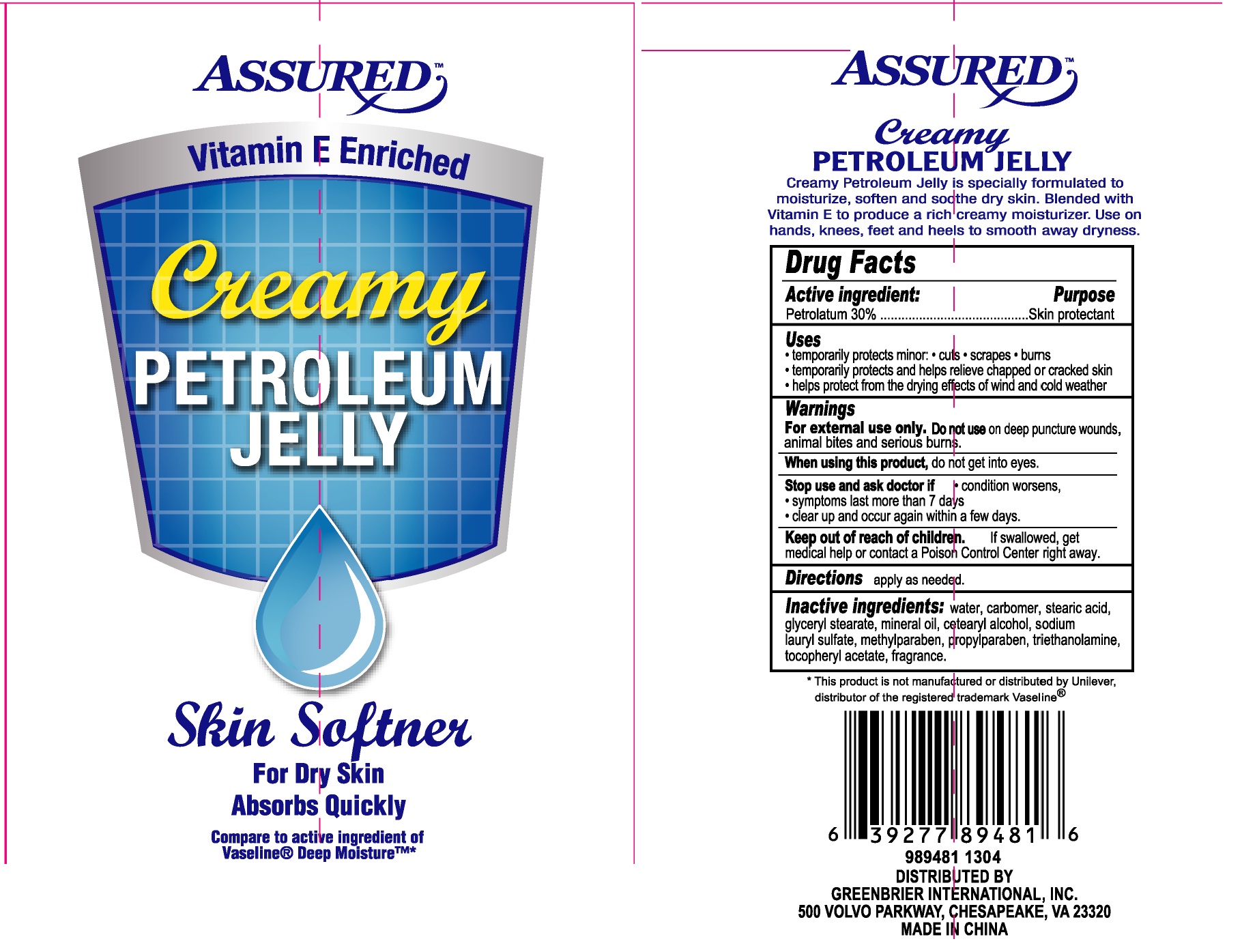 DRUG LABEL: Assured CREAMY PETROLEUM JELLY VITAMIN E ENRICHED
NDC: 33992-1210 | Form: CREAM
Manufacturer: GREENBRIER INTERNATIONAL
Category: otc | Type: HUMAN OTC DRUG LABEL
Date: 20130425

ACTIVE INGREDIENTS: PETROLATUM 30 g/100 g
INACTIVE INGREDIENTS: WATER; STEARIC ACID; GLYCERYL MONOSTEARATE; MINERAL OIL; CETOSTEARYL ALCOHOL; SODIUM LAURYL SULFATE; METHYLPARABEN; PROPYLPARABEN; TROLAMINE

Drug Fact

CREAMY

PETROLEUM JELLY

Creamy petroleum Jelly is specially formulated to moisturize, soften and soothe dry skin. Blended with Vitamin E to produce a rich creamy moisturizer. Use on hands, knees, feet and heels to smooth away dryness.

DRUG FACTS

Active Ingredient Purpose

Petrolatum 30% Skin Protectant

Purpose

Skin Protectant

INDICATIONS AND USAGE

temporarily protects minor:

cuts scrapes burns

Temporarily protects and helps relieve chapped or cracked skin

Helps protect from the drying effects of wind and cold weather

Warnings

For external use only. Do not use on deep puncture wounds, animal bites and serious burns.

When using this product, do not get into eyes

Stop use and ask doctor if

condition worsens

Symptoms last more than 7 days

clear up and occur again within a few days.

Keep out of reach of children. If swallowed, get medical help or contact a Poison Control Center right away.

DOSAGE AND ADMINISTRATION

Directions: apply as needed

Inactive ingredients:

water, carbomer, stearic acid, glyceryl stearate, mineral oil, cetearyl alcohol, sodium lauryl sulfate, methylparaben, propylparaben, triethanolamine, tocopheryl acetate, fragrance.

*This product is not manufactured or distributed by Unilever, distributor of the registered trademark Vaseline (r)

DISTRIBUTED BY:

GREENBRIER INTERNATIONAL, INC

CHESAPEAKE VA 23320

MADE IN CHINA

PACKAGE LABEL

CREAMY

PETROLEUM JELLY

VITAMIN E ENRICHED

Skin Softener

For Dry Skin

Absorbs Quickly

Net Wt. 4.5oz (127g)